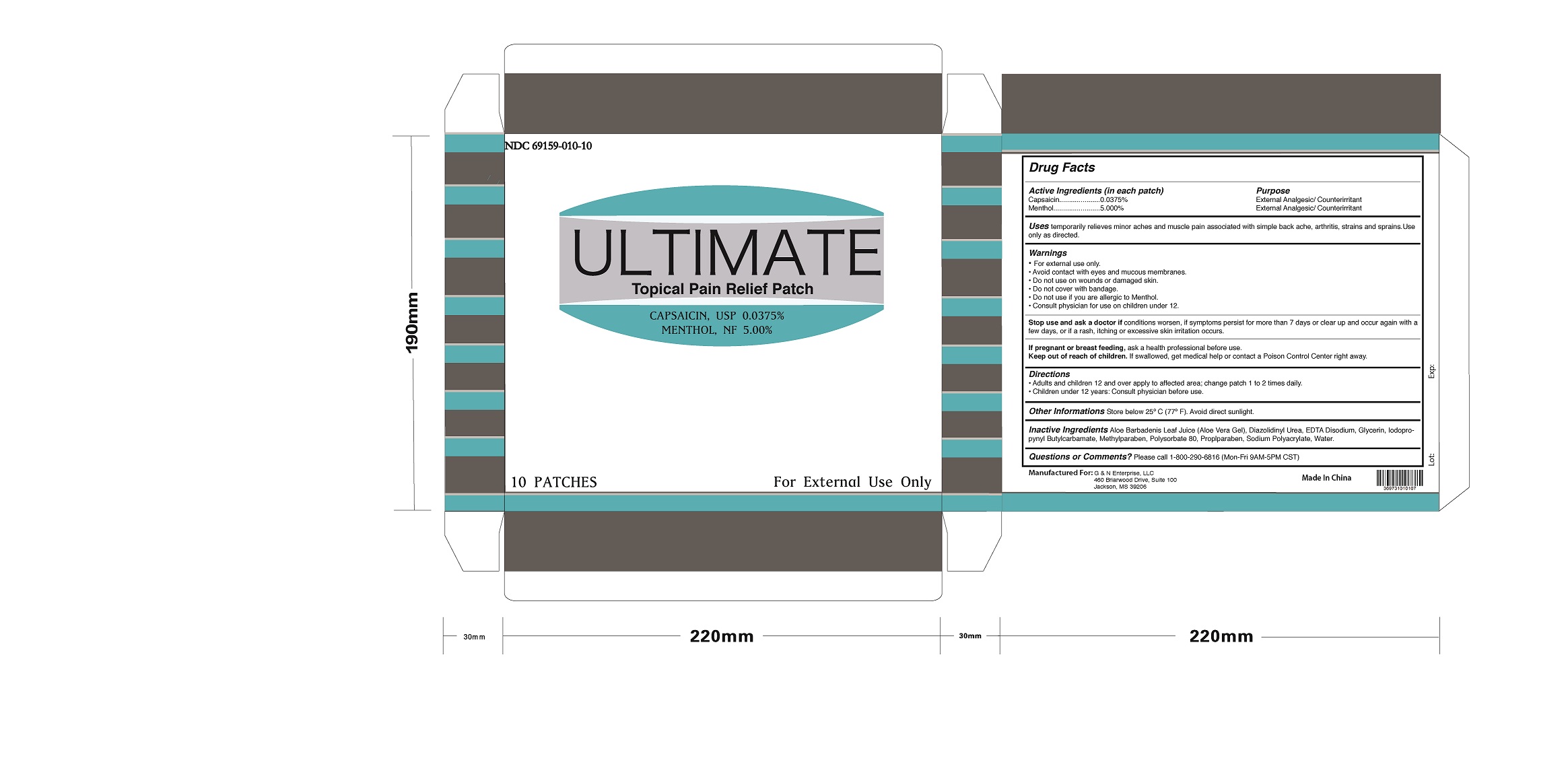 DRUG LABEL: Ultimate Topical Pain Relief Patch
NDC: 69159-910 | Form: PATCH
Manufacturer: Foshan Aqua Gel Biotech Co.,Ltd.
Category: otc | Type: HUMAN OTC DRUG LABEL
Date: 20171106

ACTIVE INGREDIENTS: MENTHOL, UNSPECIFIED FORM 5 g/100 g; CAPSAICIN 0.0375 g/100 g
INACTIVE INGREDIENTS: DIAZOLIDINYL UREA; EDETATE DISODIUM; GLYCERIN; IODOPROPYNYL BUTYLCARBAMATE; METHYLPARABEN; POLYSORBATE 80; PROPYLPARABEN; WATER; ALOE VERA LEAF; SODIUM POLYACRYLATE (2500000 MW)

Ultimate Topical Pain Relief Patch

Active Ingredients

Menthol 5.00%

Capsaicin 0.0375%

Purpose:

External Analgesic/Counterirritant

External Analgesic/Counterirritant

Uses:

Temporarily relieves minor aches and muscle pain associated with simple back ache, arthritis, strains and sprains. Use only as directed.

Warnings

- For external useonly.
- Avoid contact with eyes and mucous membranes.
- Do not use on wounds or damaged skin.
- Do not cover with bandage.
- Do not use if you are allergic to Menthol.
- Consult physician for use on children under 12.

Stop use and ask a doctor if

conditions worsen, if symptoms persist for more than 7 days or clear up and occur again with a few days, or if a rash,

itching or excessive skin irritation occurs.

If pregnant or breast feeding

ask a health professional before use.

Keep out of reach of children

If swallowed, get medical help or contact a Poison Control Center right away.

Directions

- Adults and children 12 and over apply to affected area; change patch 1 to 2 times daily
- Children under 12 years: Consult physician before use.

Other Information

Store below 25°C (77°F). Avoid direct sunilght.

Inactive Ingredients:

Aloe Barbadensis Leaf (Aloe Vera Gel) Juice, Diazolidinyl Urea, EDTA Disodium ,Glycerin, Iodopropynyl Butylcarbamate, Methylparaben, Polysorbate 80, Propylparaben, Sodium Polyacrylate, and Water.

Questions or Comments?

Please call 1-800-290-6816 (Mon-Fri 9AM-5PM CST)

Dosage and Administration

Ultimate Topical Pain Relief Patch contains 0.0375% capsaicin and 5.00% menthol